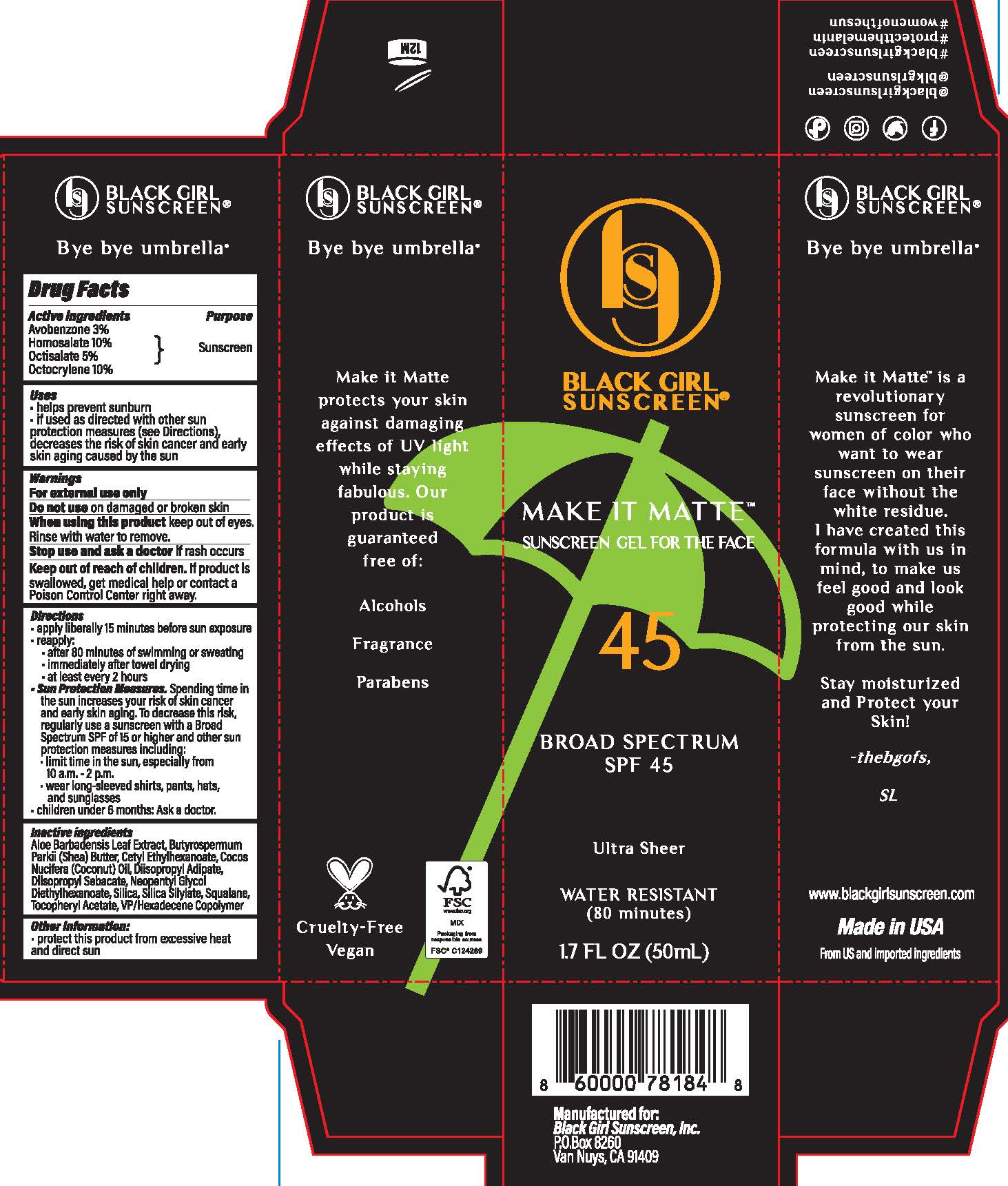 DRUG LABEL: Black Girl Sunscreen
NDC: 84204-0005 | Form: GEL
Manufacturer: Black Girl Sunscreen, LLC
Category: otc | Type: HUMAN OTC DRUG LABEL
Date: 20250115

ACTIVE INGREDIENTS: HOMOSALATE 79 mg/1 mL; OCTISALATE 39.5 mg/1 mL; AVOBENZONE 23.7 mg/1 mL; OCTOCRYLENE 39.5 mg/1 mL
INACTIVE INGREDIENTS: SHEA BUTTER; ISODODECANE; SQUALANE; ALPHA-TOCOPHEROL ACETATE; ALOE VERA LEAF; COCONUT OIL; SILICON DIOXIDE

Black Girl Sunscreen Make it Matte Broad Spectrum SPF 45

Active Ingredients

Avobenzone 3%

Homosalate 10%

Octisalate 5%

Octocrylene 5%

Purpose

Sunscreen

Uses

helps prevent sunburn

if used as directed with other sun protection measures (see Directions), decreases the risk of skin cancer and early skin aging caused by the sun

Warnings

For external use only

Do not use

on damaged or broken skin

When using this product

keep out of eyes.

Rinse with water to remove.

Stop use and ask a doctor

if rash occurs

Keep out of reach of children.

If product is swallowed, get medical help or contact a Poison Control Center right away.

Directions

apply liberally 15 minutes before sun exposure

reapply:

after 80 minutes of swimming or sweating

immediately after towel drying

at least every 2 hours

Sun Protection Measures.Spending time in the sun increases your risk of skin cancer and early skin aging. To decrease this risk, regularly use a sunscreen with a Broad Spectrum SPF of 15 or higher and other sun protection measures including:

limit time in the sun, especially from 10 a.m. - 2 p.m.

wear long-sleeved shirts, pants, hats, and sunglasses

children under 6 months: Ask a doctor.

Inactive ingredients

Aloe Barbadensis Leaf Extract, Butyrospermum Parkii (Shea) Butter, Cocos Nucifera (Coconut) Oil, Dimethicone Crosspolymer-3, Isododecane, Silica, Squalane, Tocopheryl Acetate

Other information:

protect this product from excessive heat and direct sun